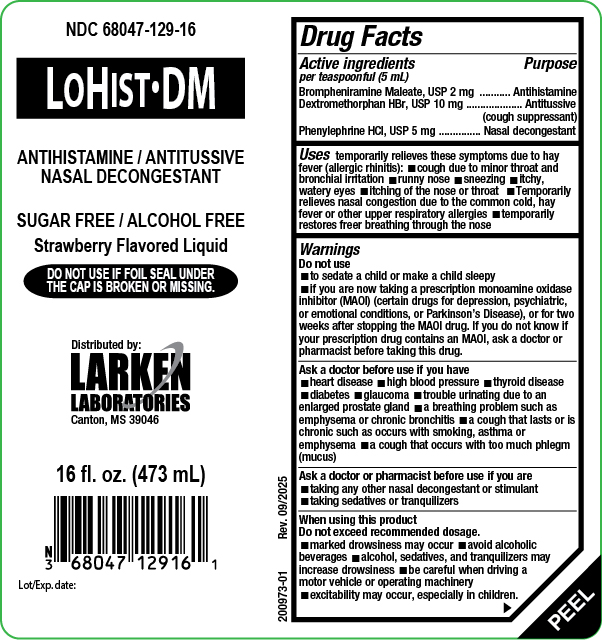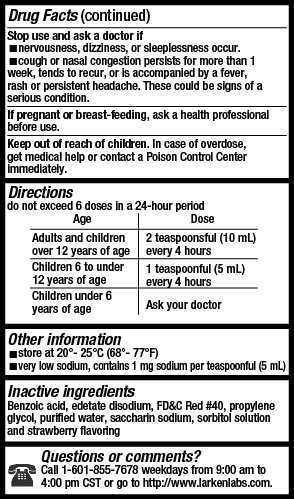 DRUG LABEL: LoHist DM
NDC: 68047-129 | Form: LIQUID
Manufacturer: Larken Laboratories, Inc.
Category: otc | Type: HUMAN OTC DRUG LABEL
Date: 20251015

ACTIVE INGREDIENTS: DEXTROMETHORPHAN HYDROBROMIDE 10 mg/5 mL; PHENYLEPHRINE HYDROCHLORIDE 5 mg/5 mL; BROMPHENIRAMINE MALEATE 2 mg/5 mL
INACTIVE INGREDIENTS: EDETATE DISODIUM; FD&C RED NO. 40; PROPYLENE GLYCOL; WATER; SACCHARIN SODIUM; SORBITOL; BENZOIC ACID

LoHist DM

Drug Facts

Active ingredients

(In each 5 mL teaspoonful)

Brompheniramine Maleate, USP 2 mg

Dextromethorphan HBr, USP 10 mg

Phenylephrine HCl, USP 5 mg

Purpose

Brompheniramine Maleate Antihistamine

Dextromethorphan HBr Antitussive (cough suppressant)

Phenylephrine HCl Nasal decongestant

Uses

Temporarily relieves these symptoms due to hay fever (allergic rhinitis):

- cough due to minor throat and bronchial irritation
- runny nose
- sneezing
- itchy, watery eyes
- itching of the nose or throat
- Temporarily relieves nasal congestion due to the common cold, hay fever or other upper respiratory allergies, or associated with sinusitis.
- Temporarily restores freer breathing through the nose

Warnings

Do not use

- to sedate a child or make a child sleepy
- if you are now taking a prescription monoamine oxidase inhibitor (MAOI) (certain drugs for depression, psychiatric, or emotional conditions, or Parkinson's disease), or for 2 weeks after stopping the MAOI drug. If you do not know if your prescription drug contains an MAOI, ask a doctor or pharmacist before taking this drug.

Ask a doctor before use if you have

- heart disease
- high blood pressure
- thyroid disease
- diabetes
- glaucoma
- trouble urinating due to an enlarged prostate gland
- a breathing problem such as emphysema or chronic bronchitis
- a cough that lasts or is chronic such as occurs with smoking, asthma or emphysema
- a cough that occurs with too much phlegm (mucus)

Ask a doctor or pharmacist before use if you are

- taking any other nasal decongestant or stimulant
- taking sedatives or tranquilizers

When using this product

Do not exceed recommended dosage.

- marked drowsiness may occur
- avoid alcoholic beverages
- alcohol, sedatives, and tranquilizers may increase drowsiness
- be careful when driving a motor vehicle or operating machinery
- excitability may occur, especially in children

Stop use and ask a doctor if

- nervousness, dizziness, or sleeplessness occur.
- cough or nasal congestion persists for more than 1 week, tends to recur, or is accompanied by a fever, rash or persistent headache. These could be signs of a serious condition.

If pregnant or breast-feeding

ask a health professional before use.

Keep out of the reach of children

In case of overdose, get medical help or contact a Poison Control Center immediately.

Directions

Do not exceed 6 doses in a 24-hour period

Age | Dose
Adults and children over 12 years of age | 2 teaspoonsful (10 mL) every 4 hours
Children 6 to under 12 years of age | 1 teaspoonful (5 mL) every 4 hours
Children under 6 years of age | Ask your doctor

Other Information

- store at 20°-25°C (68°-77°F)
- very low sodium, contains 1 mg sodium per teaspoonful (5 mL)

Inactive Ingredients

Benzoic acid, edetate disodium, FD&C Red #40, propylene glycol, purified water, saccharin sodium, sorbitol solution, and strawberry flavoring

Questions or Comments

Call 1-601-855-7678 weekdays from 9:00 am to 4:00 pm CST or go to http://www.larkenlabs.com.

Principal Display Panel

16 oz Bottle Label